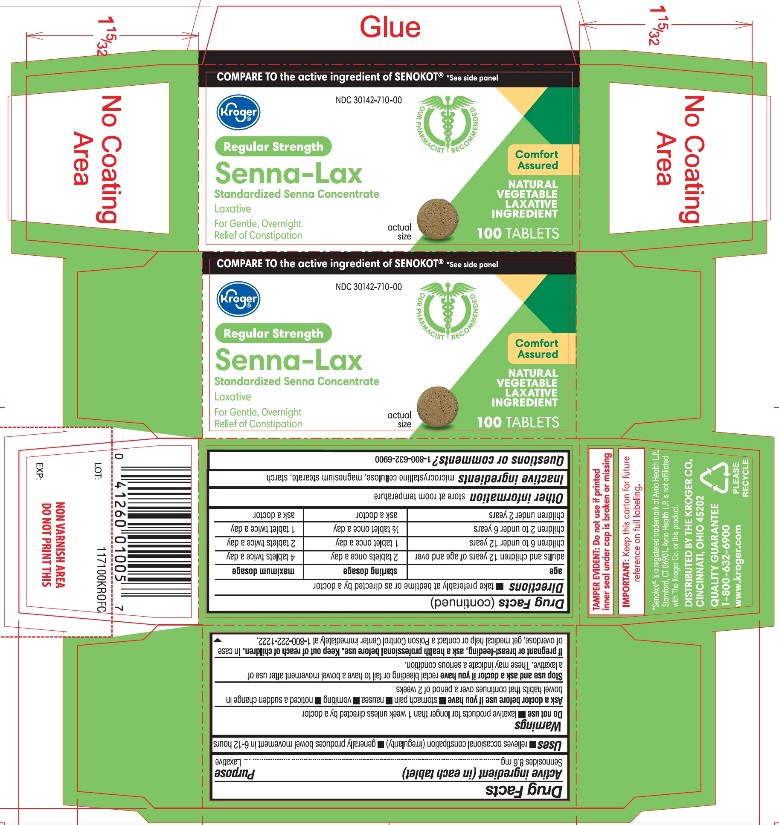 DRUG LABEL: Kroger Senna Laxative

NDC: 30142-710 | Form: TABLET
Manufacturer: KROGER COMPANY
Category: otc | Type: HUMAN OTC DRUG LABEL
Date: 20250804

ACTIVE INGREDIENTS: SENNOSIDES 8.6 mg/1 1
INACTIVE INGREDIENTS: MICROCRYSTALLINE CELLULOSE; MAGNESIUM STEARATE; STARCH, CORN

Kroger Regular Strength Senna-Lax Standardized Senna Concentrate Drug Facts

Active ingredient (in each tablet)

Sennosides 8.6 mg

Purpose

Laxative

Uses

- relieves occasional constipation (irregularity)
- generally produces a bowel movement within 6- 12 hours.

Warnings

Do not use

- laxative products for longer than 1 week unless directed by a doctor

Ask a doctor before use if you have

- stomach pain
- nausea
- vomiting
- noticed a sudden change in bowel habits that continues over a period of 2 weeks.

Stop use and ask a doctor if you have

rectal bleeding or fail to have a bowel movement after use of a laxative. These may indicate a serious condition.

If pregnant or breast-feeding,

ask a health professional before use.

Keep out of reach of children.

In case of overdose, get medical help or contact a Poison Control Center right immediately at 1-800-222-1222.

Directions

- take preferably at bedtime or as directed by a doctor

Age | starting dosage | maximum dosage
adults and children 12 years of age and over | 2 tablets once a day | 4 tablets twice a day
children 6 to under 12 years | 1 tablet once a day | 2 tablets twice a day
children 2 to under 6 years | 1/2 tablet once a day | 1 tablet twice a day
children under 2 years | ask a doctor | ask a doctor

Other information

- store at room temperature

Inactive Ingredients

microcrystalline cellulose, magnesium stearate, starch

Questions or comments?

Call 1-800-632-6900

Principal Display Panel

NDC# 30142-710-00

COMPARE TO the active ingredient of SENOKOT® *See side panel

Regular Strength

Senna-Lax

Standardized Senna Concentrate

Laxative

For Gentle Overnight relief of Constipation

Comfort Assured

NATURAL VEGETABLE LAXATIVE INGREDIENT

100 TABLETS

Senokot®.is a registered trademark of Avrio Health L.P. is not affiliated with The Kroger Co. or this product.

TAMPER EVIDENT: Do not use if printed inner seal under cap is broken or missing

IMPORTANT:Keep this carton for future reference on full labeling.

DISTRIBUTED BY THE KROGER CO.

CINCINNATI, OHIO 45202

QUALITY GUARANTEE

1-800-632-6900

www.kroger.com